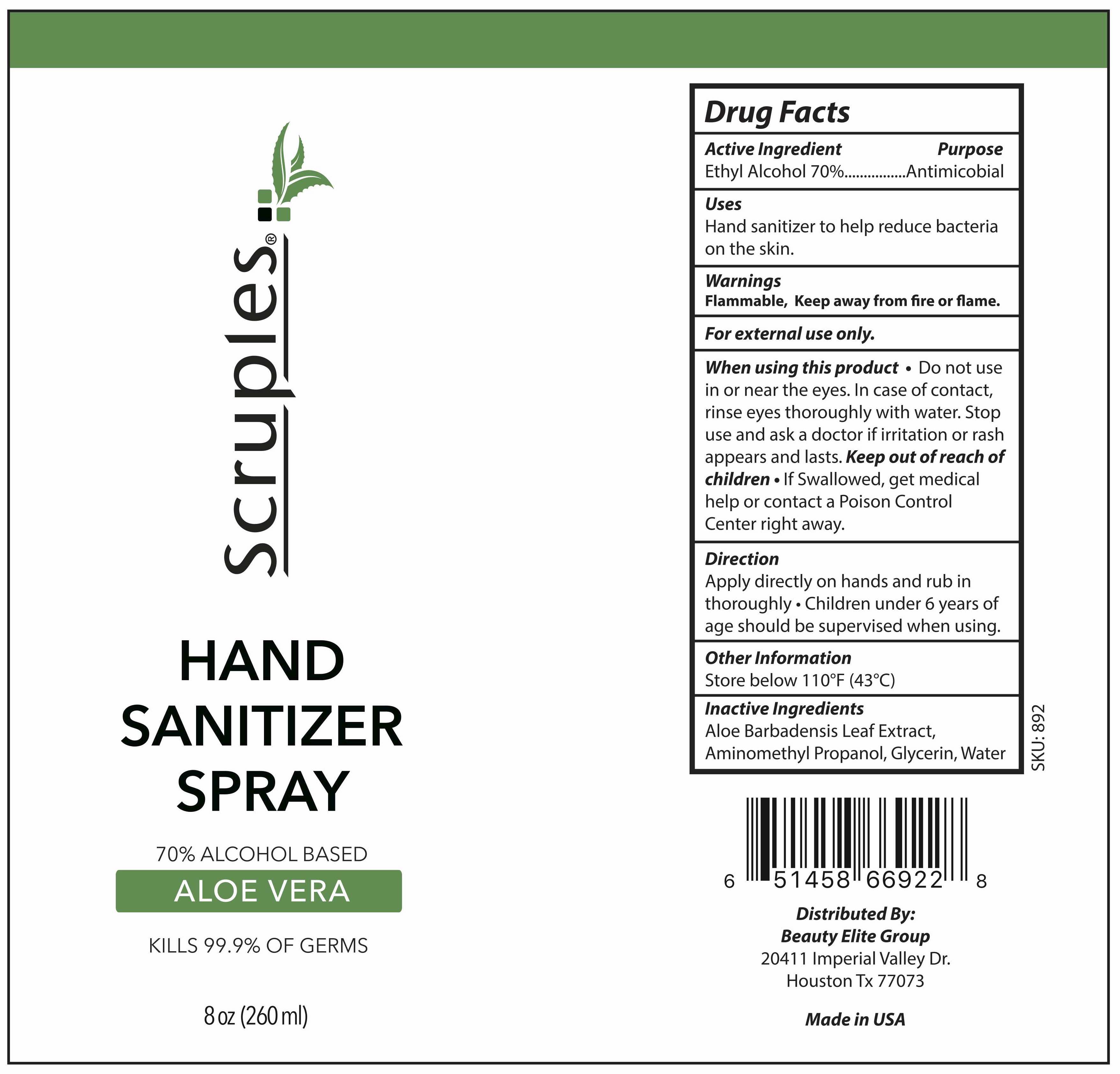 DRUG LABEL: Hand Sanitizer
NDC: 77664-922 | Form: SPRAY
Manufacturer: Beauty Elite Group
Category: otc | Type: HUMAN OTC DRUG LABEL
Date: 20200514

ACTIVE INGREDIENTS: ALCOHOL 70 mL/100 mL
INACTIVE INGREDIENTS: GLYCERIN 1.45 mL/100 mL; WATER

HAND SANITIZER SPRAY

Active Ingredient(s)

Ethyl Alcohol 70% v/v. Purpose: Antimicrobial

Purpose

Antimicrobial

Use

Hand Sanitizer to help reduce bacteria on the skin.

Warnings

For external use only. Flammable. Keep away from fire or flame

When using this product do not use in or near the eyes. In case of contact, rinse eyes thoroughly with water.
Stop use and ask a doctor if irritation or rash appears and lasts.
Keep out of reach of children. If swallowed, get medical help or contact a Poison Control Center right away.

Stop use and ask a doctor if irritation or rash appears and lasts.

Keep out of reach of children. If swallowed, get medical help or contact a Poison Control Center right away.

Directions

- Place enough product on hands to cover all surfaces. Rub hands together until dry.
- Supervise children under 6 years of age when using this product to avoid swallowing.

Other information

Store below 110F (43C)

Inactive ingredients

Aloe Barbadensis Leaf Extract, Aminomethyl Propanol, Glycerin, Water

Package Label - Principal Display Panel

236 mL NDC: 77664-922-01